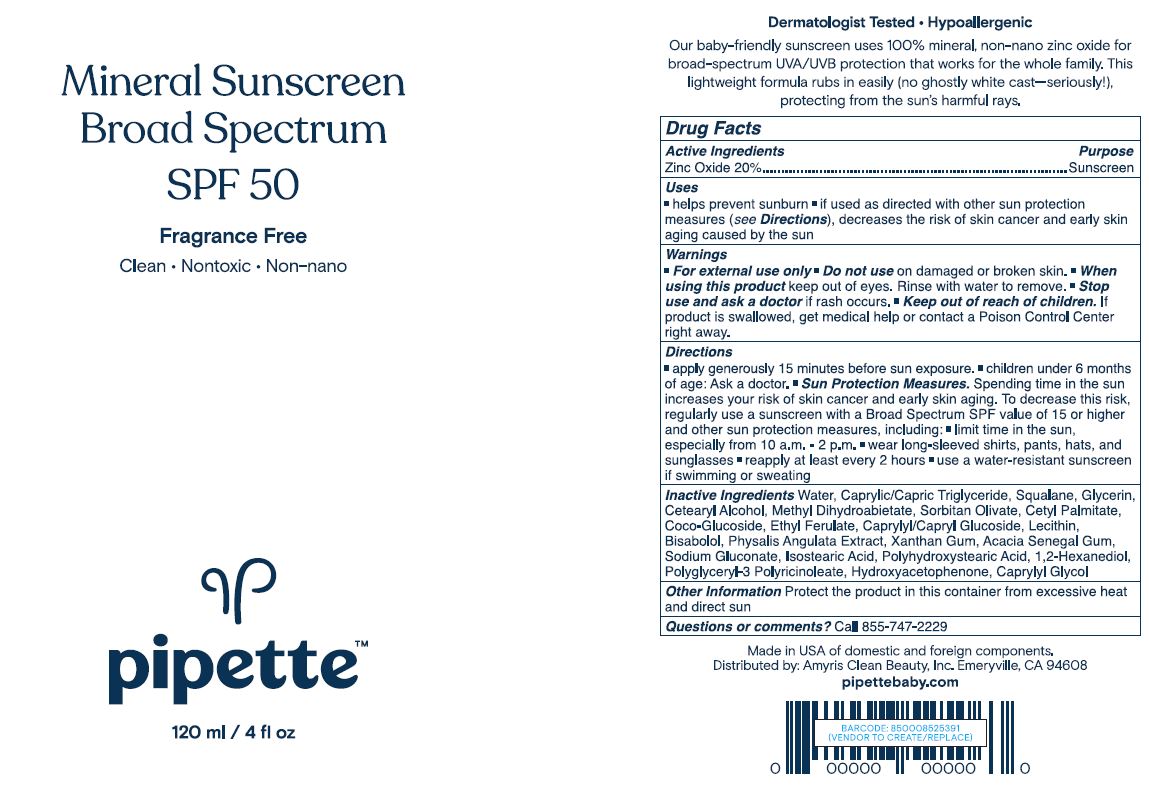 DRUG LABEL: Pipette Mineral Sunscreen Broad Spectrum SPF 50
NDC: 73517-128 | Form: LOTION
Manufacturer: Amyris, Inc
Category: otc | Type: HUMAN OTC DRUG LABEL
Date: 20220107

ACTIVE INGREDIENTS: ZINC OXIDE 200 mg/1 mL
INACTIVE INGREDIENTS: SODIUM GLUCONATE; POLYHYDROXYSTEARIC ACID (2300 MW); CETYL PALMITATE; .ALPHA.-BISABOLOL, (+/-)-; PHYSALIS ANGULATA; ACACIA; CAPRYLYL GLYCOL; METHYL DIHYDROABIETATE; ETHYL FERULATE; MEDIUM-CHAIN TRIGLYCERIDES; CETOSTEARYL ALCOHOL; COCO GLUCOSIDE; CAPRYLYL/CAPRYL OLIGOGLUCOSIDE; LECITHIN, SOYBEAN; POLYGLYCERYL-3 PENTARICINOLEATE; SORBITAN OLIVATE; XANTHAN GUM; ISOSTEARIC ACID; 1,2-HEXANEDIOL; HYDROXYACETOPHENONE; GLYCERIN; SQUALANE; WATER

Pipette Mineral Sunscreen Broad Spectrum SPF 50

Active Ingredient(s)

Zinc Oxide 20% Purpose: Sunscreen

Purpose

Sunscreen Helps prevent sunburn

Use

Helps prevent sunburn

if used as directed with other sun protection measures (see directions), decreases the risk of skin cancer and early signs of aging caused by the sun

Warnings

For external use only

Do not use on damaged or broken skin

When using this product keep out of eyes Rinse with water to remove

Stop use and ask a doctor if rash occurs

Keep out of reach of children if product is swallowed get medical help or contact Poison Control Center right away

Directions

apply generously 15 minutes before sun exposure. reapply at least every 2 hours

Sun Protection Measures

Spending time in the sun increases your risk of skin cancer and early skin aging. To decrease this risk, regularly use a sunscreen with a Broad Spectrum value of SPF 15 or higher and other sun protections measures including: limit time in the sun, especially from 10 am - 2pm

wear long-sleeved shirts, pants, hats, and sunglasses

use a water-resistant sunscreen if swimming or sweating

children under 6 months of age ask a doctor.

Other information

- protect this product from excessive heat and direct sun

Inactive ingredients

Inactive Ingredients: Water, Caprylic/Capric Triglyceride, Squalane, Glycerin, Cetearyl Alcohol, Methyl Dihydroabietate, Sorbitan Olivate, Cetyl Palmitate, Coco-Glucoside, Ethyl Ferulate, Caprylyl/Capryl Glucoside, Lecithin, Bisabolol, Physalis Angulata Extract, Xanthan Gum, Acacia Senegal Gum, Sodium Gluconate, Isostearic Acid, Polyhydroxystearic Acid, 1,2-Hexanediol, Polyglyceryl-3 Polyricinoleate, Hydroxyacetophenone, Caprylyl Glycol

Package Label - Principal Display Panel

120 mL NDC: 73517-128-01